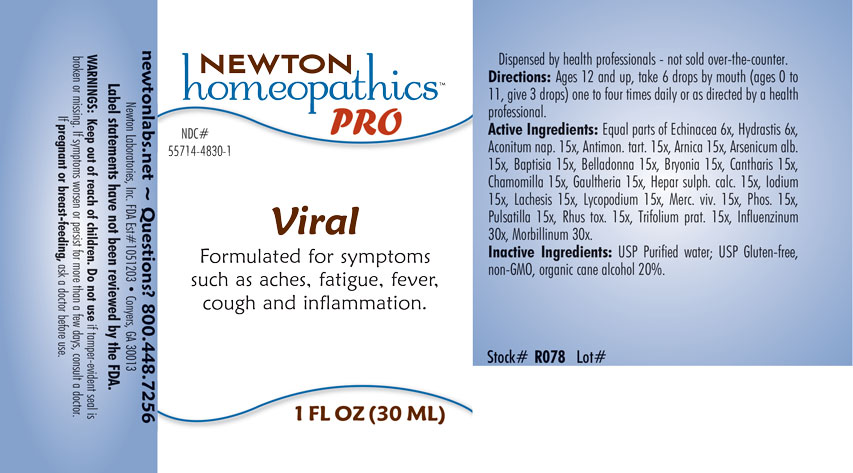 DRUG LABEL: Viral
NDC: 55714-4830 | Form: LIQUID
Manufacturer: Newton Laboratories, Inc.
Category: homeopathic | Type: HUMAN OTC DRUG LABEL
Date: 20201207

ACTIVE INGREDIENTS: MEASLES VIRUS 30 [hp_X]/1 mL; ECHINACEA, UNSPECIFIED 6 [hp_X]/1 mL; INFLUENZA A VIRUS 30 [hp_X]/1 mL; ACONITUM NAPELLUS 15 [hp_X]/1 mL; ANTIMONY POTASSIUM TARTRATE 15 [hp_X]/1 mL; ARNICA MONTANA 15 [hp_X]/1 mL; ARSENIC TRIOXIDE 15 [hp_X]/1 mL; BAPTISIA TINCTORIA ROOT 15 [hp_X]/1 mL; ATROPA BELLADONNA 15 [hp_X]/1 mL; BRYONIA ALBA ROOT 15 [hp_X]/1 mL; LYTTA VESICATORIA 15 [hp_X]/1 mL; MATRICARIA CHAMOMILLA 15 [hp_X]/1 mL; GAULTHERIA PROCUMBENS TOP 15 [hp_X]/1 mL; CALCIUM SULFIDE 15 [hp_X]/1 mL; IODINE 15 [hp_X]/1 mL; LACHESIS MUTA VENOM 15 [hp_X]/1 mL; LYCOPODIUM CLAVATUM SPORE 15 [hp_X]/1 mL; MERCURY 15 [hp_X]/1 mL; PHOSPHORUS 15 [hp_X]/1 mL; ANEMONE PULSATILLA 15 [hp_X]/1 mL; TOXICODENDRON PUBESCENS LEAF 15 [hp_X]/1 mL; TRIFOLIUM PRATENSE FLOWER 15 [hp_X]/1 mL; GOLDENSEAL 6 [hp_X]/1 mL; INFLUENZA B VIRUS 30 [hp_X]/1 mL
INACTIVE INGREDIENTS: WATER; ALCOHOL

Viral 4830L

INDICATIONS & USAGE SECTION

Formulated for symptoms such as aches, fatigue, fever, cough and inflammation.

DOSAGE & ADMINISTRATION SECTION

Directions: Ages 12 and up, take 6 drops by mouth one to four times daily or as directed by a health professional.

OTC - ACTIVE INGREDIENT SECTION

Equal parts of Echinacea 6x, Hydrastis canadensis 6x, Aconitum napellus 15x, Antimonium tartaricum 15x, Arnica montana 15x, Arsenicum album 15x, Baptisia tinctoria 15x, Belladonna 15x, Bryonia 15x, Cantharis 15x, Chamomilla 15x, Gaultheria procumbens 15x, Hepar sulphuris calcareum 15x, Iodium 15x, Lachesis mutus 15x, Lycopodium clavatum 15x, Mercurius vivus 15x, Phosphorus 15x, Pulsatilla 15x, Rhus toxicodendron 15x, Trifolium pratense 15x, Influenzinum 30x, Morbillinum 30x.

OTC - PURPOSE SECTION

Formulated for symptoms such as aches, fatigue, fever, cough and inflammation.

INACTIVE INGREDIENT SECTION

Inactive Ingredients: USP Purified Water; USP Gluten-free, non-GMO, organic cane alcohol 20%.

QUESTIONS SECTION

newtonlabs.net - Questions? 800.448.7256

Newton Laboratories, Inc. FDA Est # 1051203 Conyers, GA 30013

WARNINGS SECTION

WARNINGS: Keep out of reach of children. Do not use if tamper-evident seal is broken or missing. If symptoms worsen or persist for more than a few days, consult a doctor. If pregnant or breast-feeding, ask a doctor before use.

OTC - PREGNANCY OR BREAST FEEDING SECTION

If pregnant or breast-feeding, ask a doctor before use.

OTC - KEEP OUT OF REACH OF CHILDREN SECTION

Keep out of reach of children.